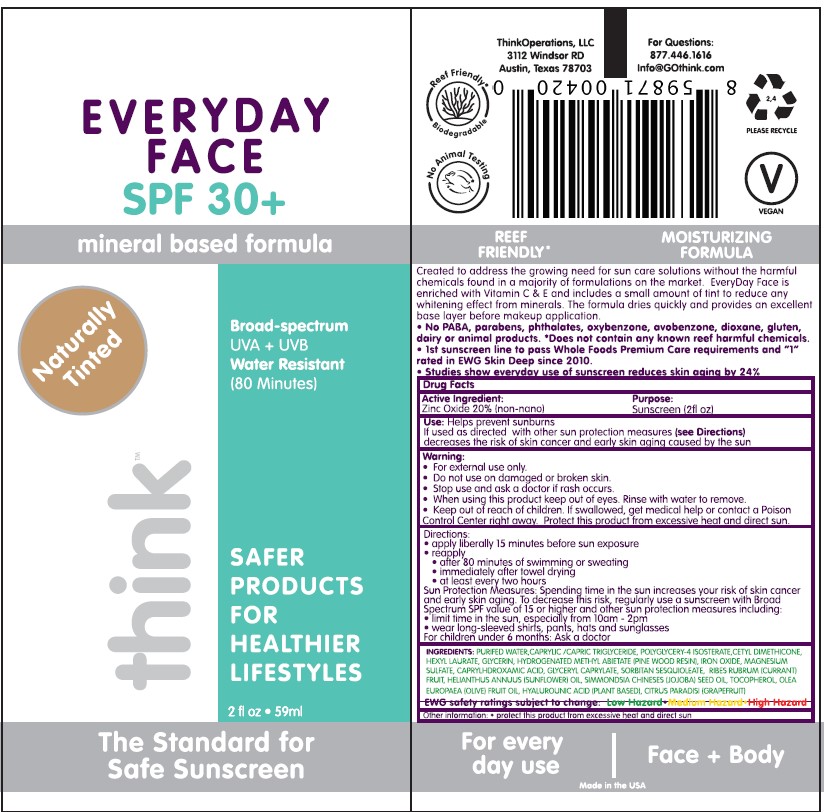 DRUG LABEL: Think Every Day Face 
NDC: 60781-1011 | Form: LOTION
Manufacturer: thinkOperations,LLC
Category: otc | Type: HUMAN OTC DRUG LABEL
Date: 20200922

ACTIVE INGREDIENTS: ZINC OXIDE 200 mg/1 mL
INACTIVE INGREDIENTS: CAPRYLHYDROXAMIC ACID; RIBES RUBRUM WHOLE; FERRIC OXIDE RED; GRAPEFRUIT; TRICAPRIN; MAGNESIUM SULFATE, UNSPECIFIED FORM; POLYGLYCERYL-4 ISOSTEARATE; JOJOBA OIL; HYALURONIC ACID; CETYL DIMETHICONE 25; SUNFLOWER OIL; TOCOPHEROL; OLIVE OIL; GLYCERYL MONOCAPRYLATE; HEXYL LAURATE; HYDROGENATED METHYL ABIETATE; TRICAPRILIN; WATER; SORBITAN SESQUIOLEATE; GLYCERIN

Think Every Day Face

Active ingredient

Zinc oxide 20%

Purpose

Sunscreen

Uses

Helps prevent sunburns if used as directed with other sun protection measures (see Directions) decreases the risk of skin cancer and early skin aging caused by the sun

Warning

For external use only

Protect this product from excessive heat and direct sun

Do not use on damaged or broken skin

Stop use and ask a doctor if rash occurs

When using this product keep out of eyes. Rinse with water to remove.

Keep out of reach of children If swallowed, get medicacl help or contact a Poison Control Center right away.

Directions

- apply liberally 15 minutes before sun exposure
- reapply
- after 80 minutes of swimming or sweating
- immediately after towel drying
- at least every two hours

Sun Protection Measures: spending time in the sun increases your risk of skin cancer and early skin aging. To decreae this risk, regularly use a sunscreen with Broad Spectrum SPF value of 15 or higher and other sun protection measures including:

- limit time in the sun, especially from 10 am - 2 pm
- wear long-sleeved shirts, pants, hats and sunglasses

For children under 6 months: Ask a doctor

INACTIVE INGREDIENT

Inactive ingredients Purified water, caprylic/capric triglyceride, polyglycery-4 isosterate, cetyl dimethicone, hexyl laurate, glycerin, hydrogenated methyl abietate (pine wood resin), iron oxide, magnesium sulfate, caprylhdroxamic acid, glyceryl caprylate, sorbitan sesquioleate, ribes rubrum (currant) fruit, helianthus annuus (sunflower) oil, simmondsia chineses (jojoba) seed oil, tocopherol, olea europaea (olive) fruit oil, hyalurounic acid (plant based), citrus paradisi (grapefruit)

Other information

protect this product from excessive heat and direct sun

For questions: 877.446.1616

PACKAGE LABEL

think

EVERYDAY FACE

SPF 30+

Broad-spectrum

UVA + UVB

Water Resistant

(80 Minutes)

Naturally Tinted

59 ml

Think Operations, LLC

3112 Windsor RD

Austin, Texas 78703

For Questions: 877.446.1616

Info@GOthink.com